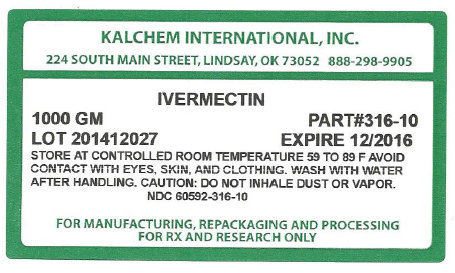 DRUG LABEL: IVERMECTIN
NDC: 60592-316 | Form: POWDER
Manufacturer: Kalchem International Inc.
Category: other | Type: BULK INGREDIENT
Date: 20160404

ACTIVE INGREDIENTS: IVERMECTIN 1 g/1 g

Ivermectin